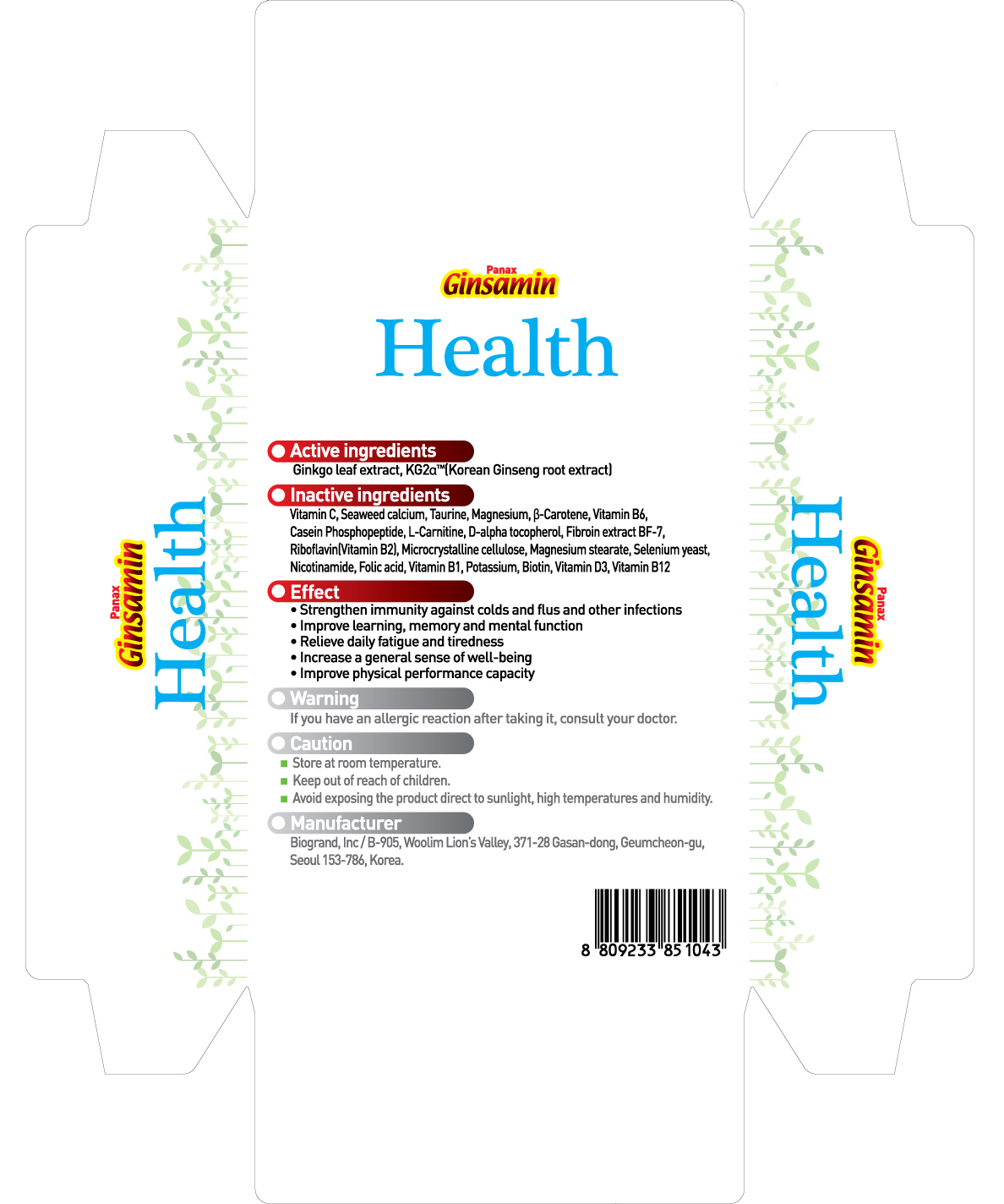 DRUG LABEL: Ginsamin Health
NDC: 44738-5001 | Form: CAPSULE
Manufacturer: Biogrand Co., Ltd
Category: otc | Type: HUMAN OTC DRUG LABEL
Date: 20100307

ACTIVE INGREDIENTS: GINKGO 90 mg/300 mg; ASIAN GINSENG 75 mg/300 mg

Drug Facts

Active Ingredients: Ginkgo Leaf extract, Panax Ginseng

DESCRIPTION

Product name
Panax Ginsamin Health
Active ingredients
Ginkgo leaf extract, Korean ginseng root extract
Inactive ingredients
seaweed calcium, casein phosphopeptide, L-carnitine, vitamin C, D-alpha tocopherol, vitamin B1,
vitamin B6, vitamin B12, vitamin B2, microcrystalline cellulose, magnesium stearate, selenium yeast,
taurine, biotin, nicotinamide, magnesium, B-carotene, folic acid
Effect
• improve learning and memory, cognitive function and concentration
• support mild memory problems associated with aging
• protect the brain from various stress
• strengthen immunity against colds and flus and other infections
• improve physical performance capacity
Warning
If you have an allergic reaction after taking it, consult your doctor
Caution
• Store at room temperature.
• Keep out of reach of children.
• Avoid exposing the product direct to sunlight, high temperatures and humidity.
• Manufacturer
Manufacturer
Biogrand, lnc / B-905, Woolim Lion’s Valley, 371-28 Gasan-dong, Geumcheon-gu, Seoul 153-786, Korea